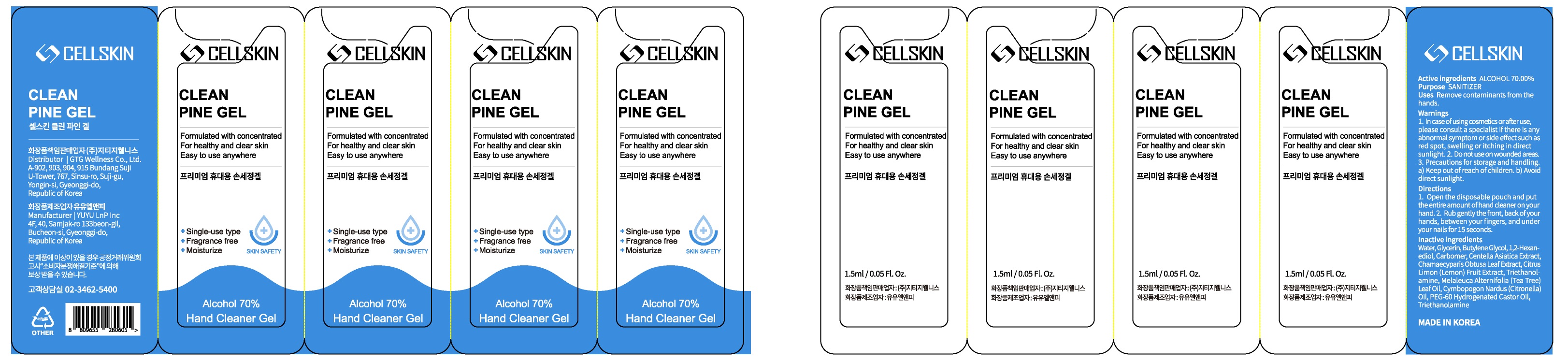 DRUG LABEL: CELLSKIN CLEAN PINE
NDC: 71080-0020 | Form: GEL
Manufacturer: GTG Wellness Co., Ltd.
Category: otc | Type: HUMAN OTC DRUG LABEL
Date: 20200713

ACTIVE INGREDIENTS: ALCOHOL 1.05 mL/1.5 mL
INACTIVE INGREDIENTS: Water; Glycerin; Butylene Glycol; 1,2-Hexanediol; CARBOMER HOMOPOLYMER, UNSPECIFIED TYPE; CENTELLA ASIATICA WHOLE; TROLAMINE

ACTIVE INGREDIENT

ALCOHOL 70.00%

INACTIVE INGREDIENTS

Water, Glycerin, Butylene Glycol, 1,2-Hexanediol, Carbomer, Centella Asiatica Extract, Chamaecyparis Obtusa Leaf Extract, Citrus Limon (Lemon) Fruit Extract, Triethanolamine, Melaleuca Alternifolia (Tea Tree) Leaf Oil, Cymbopogon Nardus (Citronella) Oil, PEG-60 Hydrogenated Castor Oil, Triethanolamine

PURPOSE

SANITIZER

WARNINGS

1. In case of using cosmetics or after use, please consult a specialist if there is any abnormal symptom or side effect such as red spot, swelling or itching in direct sunlight.
2. Do not use on wounded areas.
3. Precautions for storage and handling
a) Keep out of reach of children.
b) Avoid direct sunlight.

KEEP OUT OF REACH OF CHILDREN

Uses

Remove contaminants from the hands.

Directions

1. Open the disposable pouch and put the entire amount of hand cleaner on your hand.

2. Rub gently the front, back of your hands, between your fingers, and under your nails for 15 seconds.